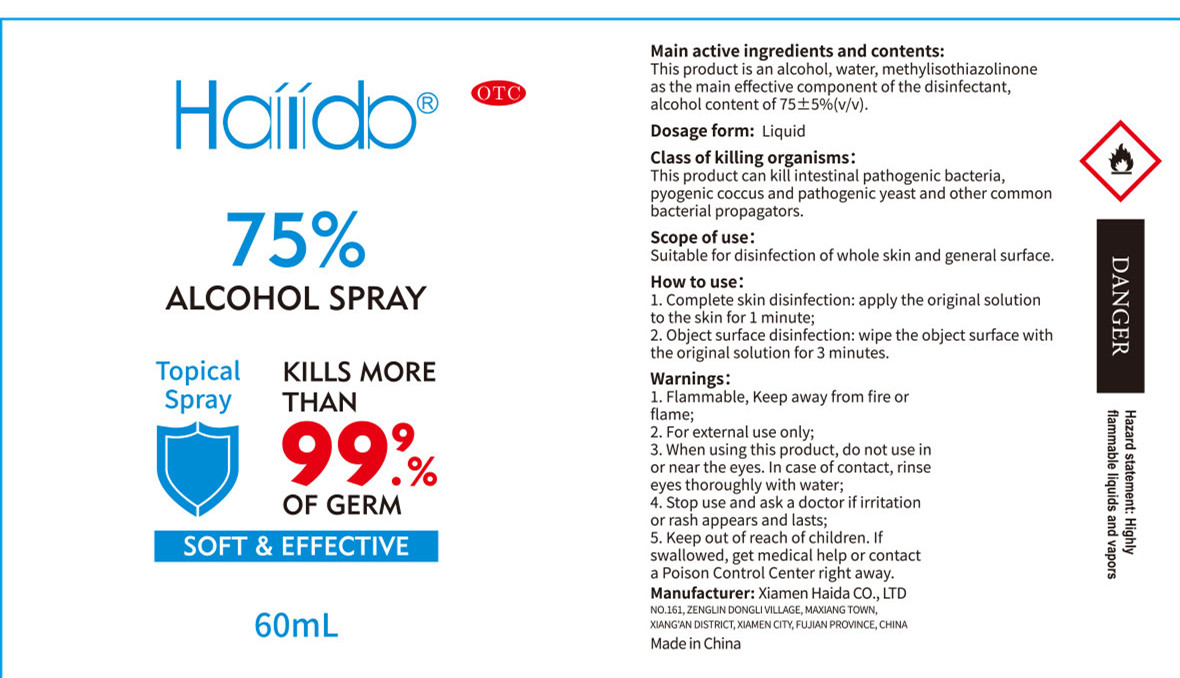 DRUG LABEL: 75% Alcohol
NDC: 52897-002 | Form: SPRAY
Manufacturer: Xiamen Haida Co., Ltd
Category: otc | Type: HUMAN OTC DRUG LABEL
Date: 20200426

ACTIVE INGREDIENTS: ALCOHOL 45 mL/60 mL
INACTIVE INGREDIENTS: METHYLISOTHIAZOLINONE; WATER

DOSAGE AND ADMINISTRATION

Flammable, Keep away from fire or flame.

INACTIVE INGREDIENT

Water

Methylisothiazolinone

INDICATIONS AND USAGE

1. Complete skin disinfection: apply the original solution to the skin for 1 minute;
2. Object surface disinfection: wipe the object surface with the original solution for 3 minutes.

ACTIVE INGREDIENT

Alcohol

keep out of children

PURPOSE

Disinfection
Sterilization

WARNINGS

1. Flammable, Keep away from fire or flame;
2. For external use only;
3. When using this product, do not use in or near the eyes. In case of contact, rinse eyes thoroughly with water;
4. Stop use and ask a doctor if irritation or rash appears and lasts;
5. Keep out of reach of children. If swallowed, get medical help or contact a Poison Control Center right away.